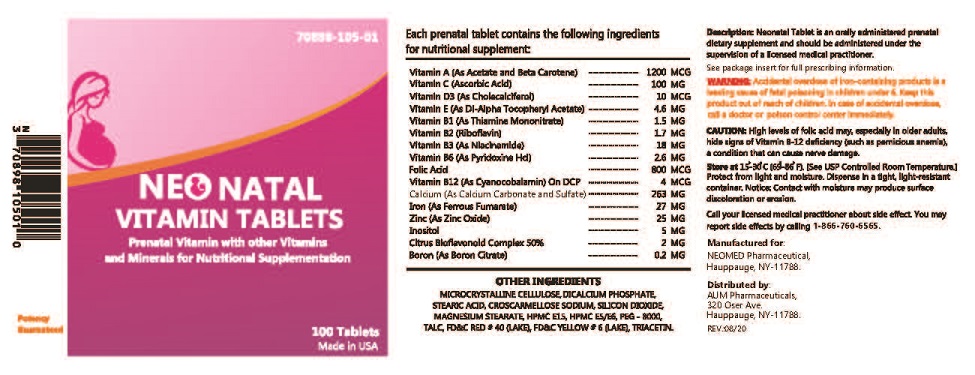 DRUG LABEL: NEONATAL VITAMIN
NDC: 70898-105 | Form: TABLET
Manufacturer: NEOMED PHARMACEUTICAL
Category: other | Type: DIETARY SUPPLEMENT
Date: 20200918

ACTIVE INGREDIENTS: VITAMIN A 1200 ug/1 1; ASCORBIC ACID 100 mg/1 1; CHOLECALCIFEROL 10 ug/1 1; .ALPHA.-TOCOPHEROL ACETATE 4.6 mg/1 1; THIAMINE 1.5 mg/1 1; RIBOFLAVIN 1.7 mg/1 1; NIACINAMIDE 1.8 mg/1 1; PYRIDOXINE HYDROCHLORIDE 2.6 mg/1 1; FOLIC ACID 800 ug/1 1; CYANOCOBALAMIN 4 ug/1 1; FERROUS FUMARATE 27 mg/1 1; INOSITOL 5 mg/1 1; CITRUS BIOFLAVONOIDS 2 mg/1 1; CALCIUM 263 mg/1 1; BORON 0.2 mg/1 1; ZINC OXIDE 25 mg/1 1
INACTIVE INGREDIENTS: CROSCARMELLOSE SODIUM; MICROCRYSTALLINE CELLULOSE; CALCIUM PHOSPHATE, DIBASIC, ANHYDROUS; STEARIC ACID; SILICON DIOXIDE; TITANIUM DIOXIDE; MAGNESIUM STEARATE; TALC; POLYETHYLENE GLYCOL 8000; HYPROMELLOSES; TRIACETIN; SUCROSE; FD&C RED NO. 40; FD&C YELLOW NO. 6

NEONATAL VITAMIN TABLETS
Prenatal Vitamin With Other Vitamins & Minerals For Nutritional Supplementation

STATEMENT OF IDENTITY

SUPPLEMENT FACTS:

Serving Size: One Tablet

Each Tablet contains:
Vitamin A (as acetate, beta carotene) |  | 1200 mcg
Vitamin D3 (as cholecalciferol) |  | 10 mcg
Vitamin E (as dl-alpha topcopheryl acetate) |  | 4.6 mg
Vitamin C (Ascorbic acid) |  | 100 mg
Vitamin B1 (as thiamine HCl) |  | 1.5 mg
Vitamin B2 (as riboflavin) |  | 1.7 mg
Vitamin B3 (as niacinamide) |  | 1.8 mg
Vitamin B6 (as pyridoxine HCl) |  | 2.6 mg
Folic acid |  | 800 mcg
Vitamin B12 (as cyanocobalamin) |  | 4 mcg
Iron (as ferrous fumarate) |  | 27 mg
Citrus bioflavonoids complex 50% bio flavonoids |  | 2 mg
Calcium (as carbonate sulfate) |  | 263 mg
Zinc (as zinc oxide) |  | 25 mg
Boron (as boron citrate) |  | 0.2 mg
Inositol |  | 5 mg

Other Ingredients: Dibasic calcium phosphate, microcrystalline croscarmellose sodium, stearic acid, silicon dioxide, titanium dioxide (as color), polyethylene glycol, sucrose, magnesium stearate, talc,triacetin, HPMC E15,HPMC E5/E6,FD&C RED #40 (LAKES),FD&C YELLOW # 6 (LAKE)

WARNINGS

WARNING: Accidental overdose of iron-containing products is a leading cause of fatal poisoning in children under 6. Keep this product out of reach of children. In case of accidental overdose, call a doctor or poison control center immediately.

DOSAGE & ADMINISTRATION

As with any supplement, if you are pregnant, nursing, or taking medication, consult your doctor before use.

The safe upper limit for daily intake of folic acid is 1000 mcg (1 mg).

Do not take Prenatal with other multivitamin formulas unless recommended by your doctor.

IMPORTANT INFORMATION

Long-term intake of high levels of vitamin A (excluding that sourced from beta-carotene) may increase the risk of osteoporosis in adults. Do not take this product if taking other vitamin A supplements.

Information for Patients

Patients should be counseled to disclose all medical conditions, including use of all medications, vitamins and supplements, pregnancy, and breastfeeding.

Pediatric Use

Not recommended for pediatric use.

HEALTH CLAIM

HOW SUPPLIED

NEONATAL VITAMIN ; available in bottles of 100 Tablets. 70898-105-01

SAFE HANDLING WARNING

Store at room temperature.
Avoid excessive heat above 40°C (104°F.)

QUESTIONS? COMMENTS?

Manufactured for:
NEOMED Pharmaceutical,
Hauppauge, NY-11788.

REV.:08/20

Distributed by:
AUM Pharmaceuticals,
320 Oser Ave.

Hauppauge, NY-11788.

DISCLAIMER: This drug has not been found by FDA to be safe and effective, and this labeling has not been approved by FDA. For further information about unapproved drugs, click here.